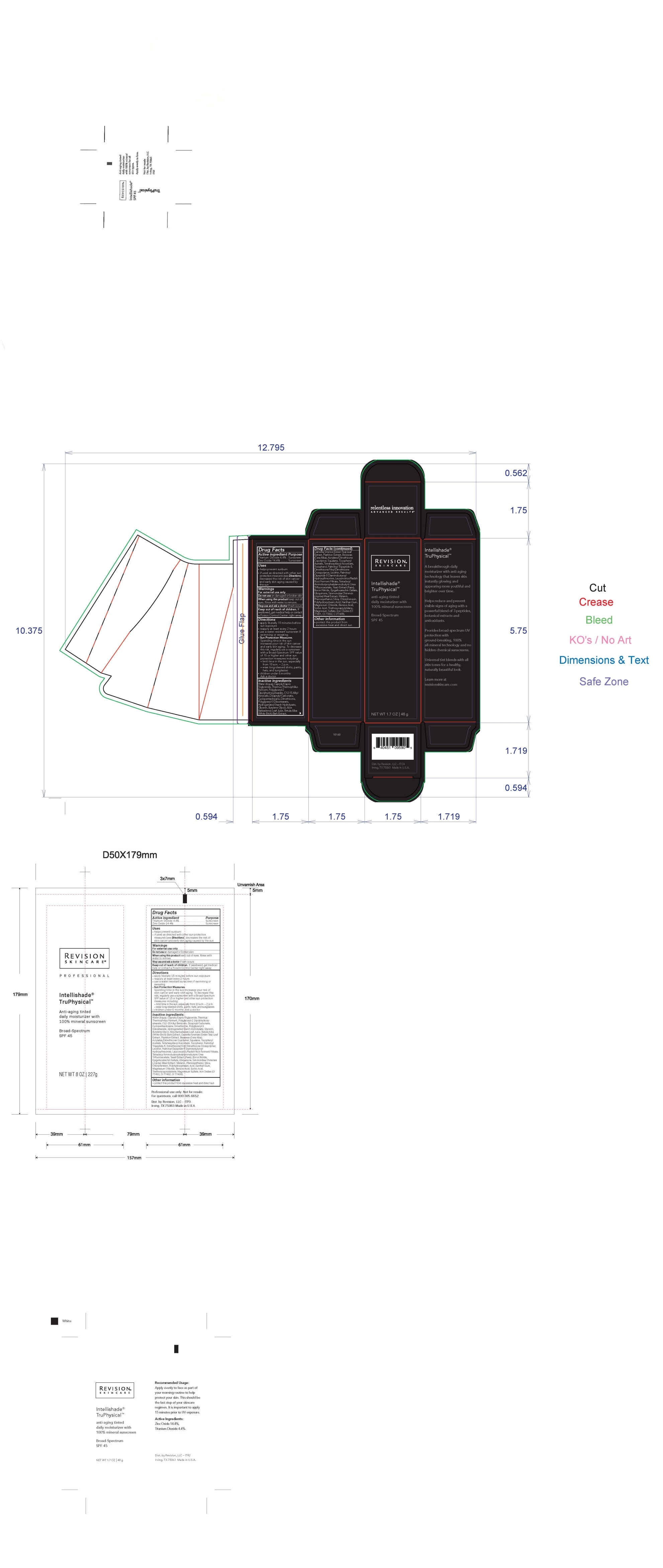 DRUG LABEL: Intellishade TruPhysical SPF 45
NDC: 64651-1003 | Form: LOTION
Manufacturer: Revision, LLC
Category: otc | Type: HUMAN OTC DRUG LABEL
Date: 20260113

ACTIVE INGREDIENTS: TITANIUM DIOXIDE 4.4 g/100 g; ZINC OXIDE 14.4 g/100 g
INACTIVE INGREDIENTS: MAGNESIUM CHLORIDE; BENZOIC ACID; SORBIC ACID; TRIETHOXYCAPRYLYLSILANE; MAGNESIUM SULFATE HEPTAHYDRATE; WATER; MEDIUM-CHAIN TRIGLYCERIDES; THERMUS THERMOPHILUS; POLYGLYCERYL-2 DIPOLYHYDROXYSTEARATE; ALKYL (C12-15) BENZOATE; DICAPRYLYL CARBONATE; CYCLOMETHICONE 5; DIMETHICONE; POLYGLYCERYL-3 DIISOSTEARATE; SORBITOL; GLYCERIN; BUTYLENE GLYCOL; ALOE VERA LEAF; WHITE WAX; SQUALANE; .ALPHA.-TOCOPHEROL ACETATE, DL-; TETRAHEXYLDECYL ASCORBATE; .ALPHA.-TOCOPHEROL; PALMITOYL TRIPEPTIDE-5; DIMETHICONE/VINYL DIMETHICONE CROSSPOLYMER (SOFT PARTICLE); LECITHIN, SOYBEAN; PALMITOYLLYSYLVALYLDIAMINOBUTYROYLTHREONINE; LEUCONOSTOC/RADISH ROOT FERMENT FILTRATE; YEAST, UNSPECIFIED; BORON NITRIDE; EPIGALLOCATECHIN GALLATE; UBIQUINONE Q2; MELANIN SYNTHETIC (TYROSINE, PEROXIDE); PHENOXYETHANOL; SILICON DIOXIDE; CHLORPHENESIN; POLYHYDROXYSTEARIC ACID (2300 MW); XANTHAN GUM

Intellishade TruPhysical SPF 45

1.7oz Revision Intellishade® TruePhysical

ITP_carton_retail_ITC6_V2_OL.jpg

ITP_retail_tube_ITR6_V2_OL.jpg

Intellishade®
TruPhysical

anti-aging tinted
daily moisturizer

with 100% mineral sunscreen

Broad-Spectrum
SPF 45

Moisturize & Protect

Net Wt

1.7 Oz 48g

Active ingredient Purpose
Zinc Oxide 14.4% ......... Sunscreen
Titanium Dioxide 4.4% . Sunscreen

Uses
• helps prevent sunburn
• if used as directed with other sun protection measures (see Directions),
decreases the risk of skin cancer and early skin aging caused by the sun

Warnings
For external use only

Do not useon damaged or broken skin

WHEN USING

When using this productkeep out of eyes. Rinse with water to remove.

Stop use and ask a doctor ifrash occurs

Keep out of reach of children.If swallowed, get medical help or contact
a Poison Control Center right away.

Directions
• apply liberally 15 minutes before sun exposure
• reapply at least every 2 hours
• use a water resistant sunscreen if swimming or sweating
• Sun Protection Measures.
Spending time in the sun increases your risk of skin cancer and early skin aging.
To decrease this risk, regularly use a sunscreen with a Broad-Spectrum SPF value
of 15 or higher and other sun protection measures including:
• limit time in the sun, especially from 10 a.m. – 2 p.m.
• wear long-sleeved shirts, pants, hats, and sunglasses
• children under 6 months: Ask a doctor

INACTIVE INGREDIENT

Inactive ingredientsWater (Aqua), Caprylic/Capric Triglyceride, Thermus Thermophillus Ferment, Polyglyceryl-2 Dipolyhydroxystearate, C12-15 Alkyl Benzoate, Dicaprylyl Carbonate, Cyclopentasiloxane, Dimethicone, Polyglyceryl-3 Diisostearate, Glycerin, Hydrogenated Starch Hydrolysate, Butylene Glycol, Aloe Barbadensis Leaf Juice, Betula Alba Bark Extract, Camellia Sinensis Leaf Extract, Plankton Extract, Beeswax (Cera Alba), Acrylates/Dimethicone Copolymer, Squalane, Tocopheryl Acetate, Tetrahexyldecyl Ascorbate, Tocopherol, Palmitoyl Tripeptide-5, Dimethicone/Vinyl Dimethicone Crosspolymer, Lecithin, Palmitoyl Dipeptide-5 Diaminobutyroyl Hydroxythreonine, Leuconostoc/Radish Root Ferment Filtrate, Tetradecyl Aminobutyroylvalylaminobutyric Urea Acetate, Yeast Extract (Faex), Boron Nitride, Epigallocatechin Gallate, Ubiquinone, Simmondsia Chinensis (Jojoba) Meal Extract, Melanin, Phenoxyethanol, Silica, Chlorphenesin, Polyhydroxystearic Acid, Xanthan Gum, Magnesium Chloride, Benzoic Acid, Sorbic Acid, Triethoxycaprylylsilane, Magnesium Sulfate, Iron Oxides (CI 77491, CI 77492, CI 77499)

Other information
• protect this product from excessive heat and direct sun

Dist. by Revision, LP

Irving TX, 75063 Made in U.S.A.

8oz Revision Intellishade® Tru Physical

ITP_pro_tube_ITP6_V1_OL.jpg

Intellishade®

TruPhysical

Anti-aging tinted

daily moisturizer with

100% mineral sunscreen

Broad-Spectrum

SPF 45

Net Wt

8Oz 227g

Active ingredient Purpose
Zinc Oxide 14.4% ......... Sunscreen
Titanium Dioxide 4.4% . Sunscreen

Uses
• helps prevent sunburn
• if used as directed with other sun protection measures (see Directions),
decreases the risk of skin cancer and early skin aging caused by the sun

Warnings

For external use only

When using this product keep out of eyes. Rinse wilth water to remove.

Stop use and ask a doctor if rash occurs

Keep out of reach of children.If swallowed, get medical help or contact
a Poison Control Center right away.

Do not used on damaged or broken skin

Directions
• apply liberally 15 minutes before sun exposure
• reapply at least every 2 hours
• use a water resistant sunscreen if swimming or sweating
• Sun Protection Measures.
Spending time in the sun increases your risk of skin cancer and early skin aging.
To decrease this risk, regularly use a sunscreen with a Broad-Spectrum SPF value
of 15 or higher and other sun protection measures including:
• limit time in the sun, especially from 10 a.m. – 2 p.m.
• wear long-sleeved shirts, pants, hats, and sunglasses
• children under 6 months: Ask a doctor

INACTIVE INGREDIENT

Inactive ingredients Water (Aqua), Caprylic/Capric Triglyceride, Thermus Thermophillus Ferment, Polyglyceryl-2 Dipolyhydroxystearate, C12-15 Alkyl Benzoate, Dicaprylyl Carbonate, Cyclopentasiloxane, Dimethicone, Polyglyceryl-3 Diisostearate, Glycerin, Hydrogenated Starch Hydrolysate, Butylene Glycol, Aloe Barbadensis Leaf Juice, Betula Alba Bark Extract, Camellia Sinensis Leaf Extract, Plankton Extract, Beeswax (Cera Alba), Acrylates/Dimethicone Copolymer, Squalane, Tocopheryl Acetate, Tetrahexyldecyl Ascorbate, Tocopherol, Palmitoyl Tripeptide-5, Dimethicone/Vinyl Dimethicone Crosspolymer, Lecithin, Palmitoyl Dipeptide-5 Diaminobutyroyl Hydroxythreonine, Leuconostoc/Radish Root Ferment Filtrate, Tetradecyl Aminobutyroylvalylaminobutyric Urea Acetate, Yeast Extract (Faex), Boron Nitride, Epigallocatechin Gallate, Ubiquinone, Simmondsia Chinensis (Jojoba) Meal Extract, Melanin, Phenoxyethanol, Silica, Chlorphenesin, Polyhydroxystearic Acid, Xanthan Gum, Magnesium Chloride, Benzoic Acid, Sorbic Acid, Triethoxycaprylylsilane, Magnesium Sulfate, Iron Oxides (CI 77491, CI 77492, CI 77499)

Other information
• protect this product from excessive heat and direct sun

Dist. by Revision, LP

Irving TX, 75063 Made in U.S.A.

DOSAGE AND ADMINISTRATION

apply liberally 15 minutes before sun exposure
reapply at least every two hours
use a water resistant sunscreen if swimming or sweating

PURPOSE

Anti-aging tinted daily moisturizer with 100% mineral sunscreen

Broad Spectrum

SPF 45